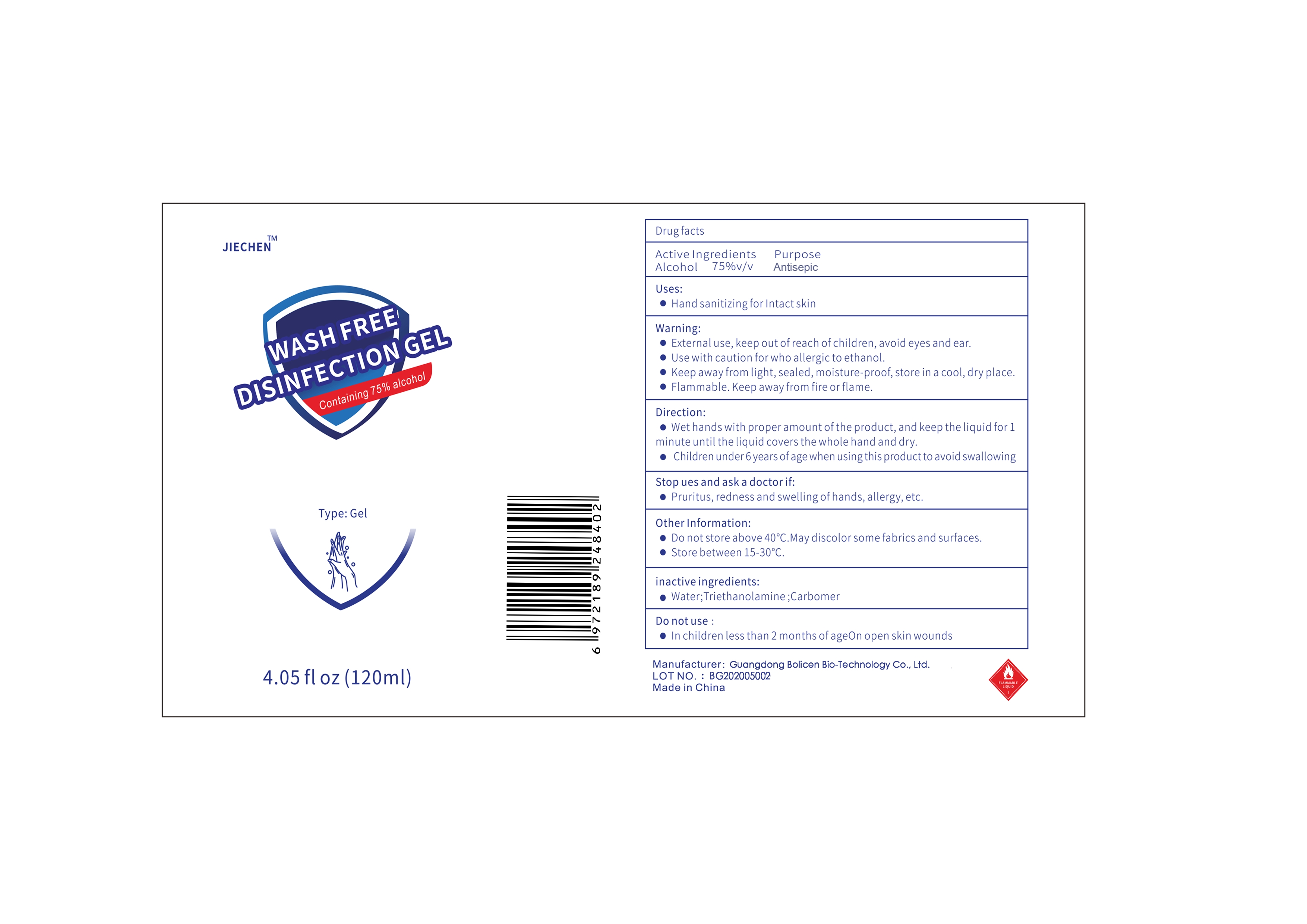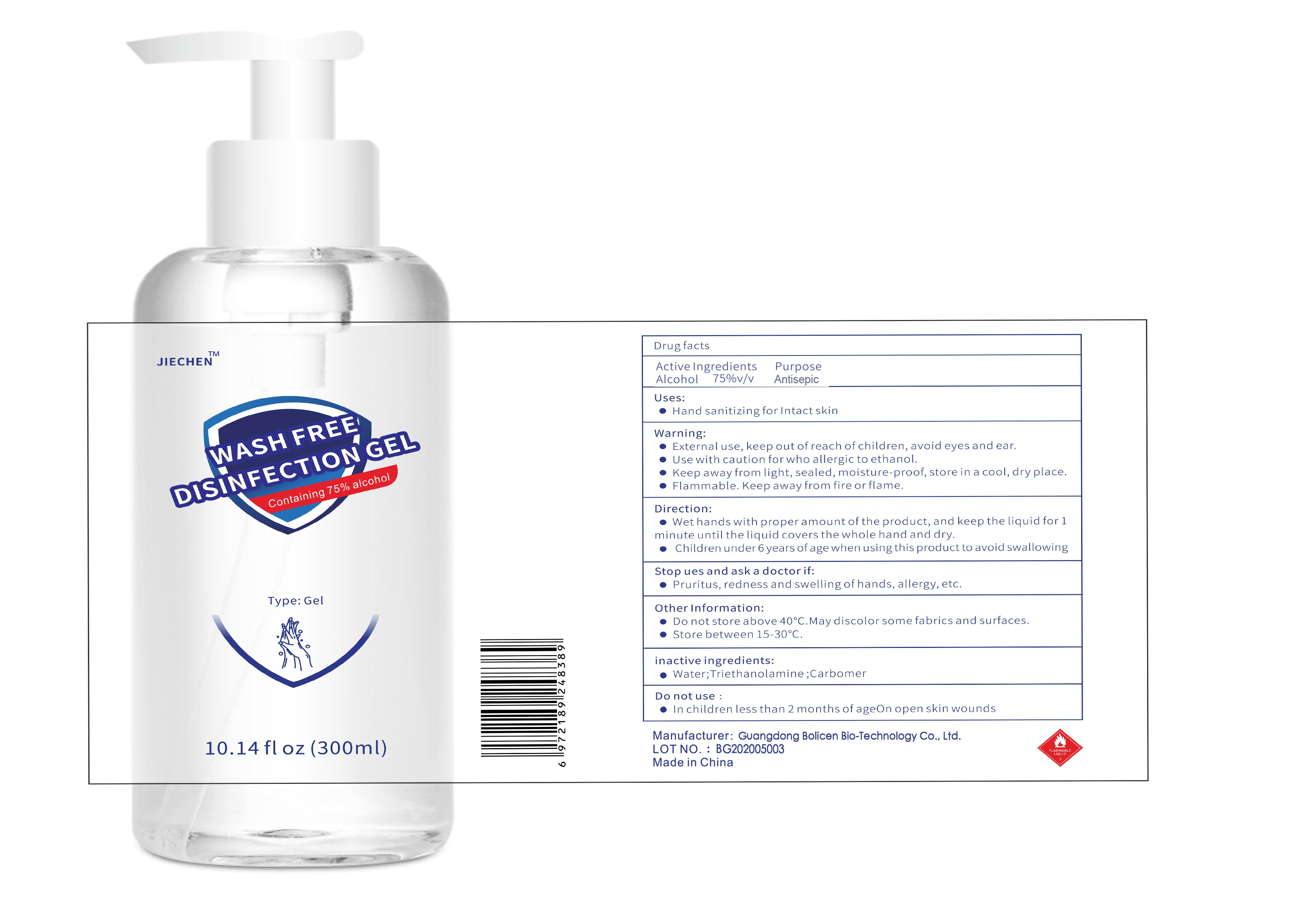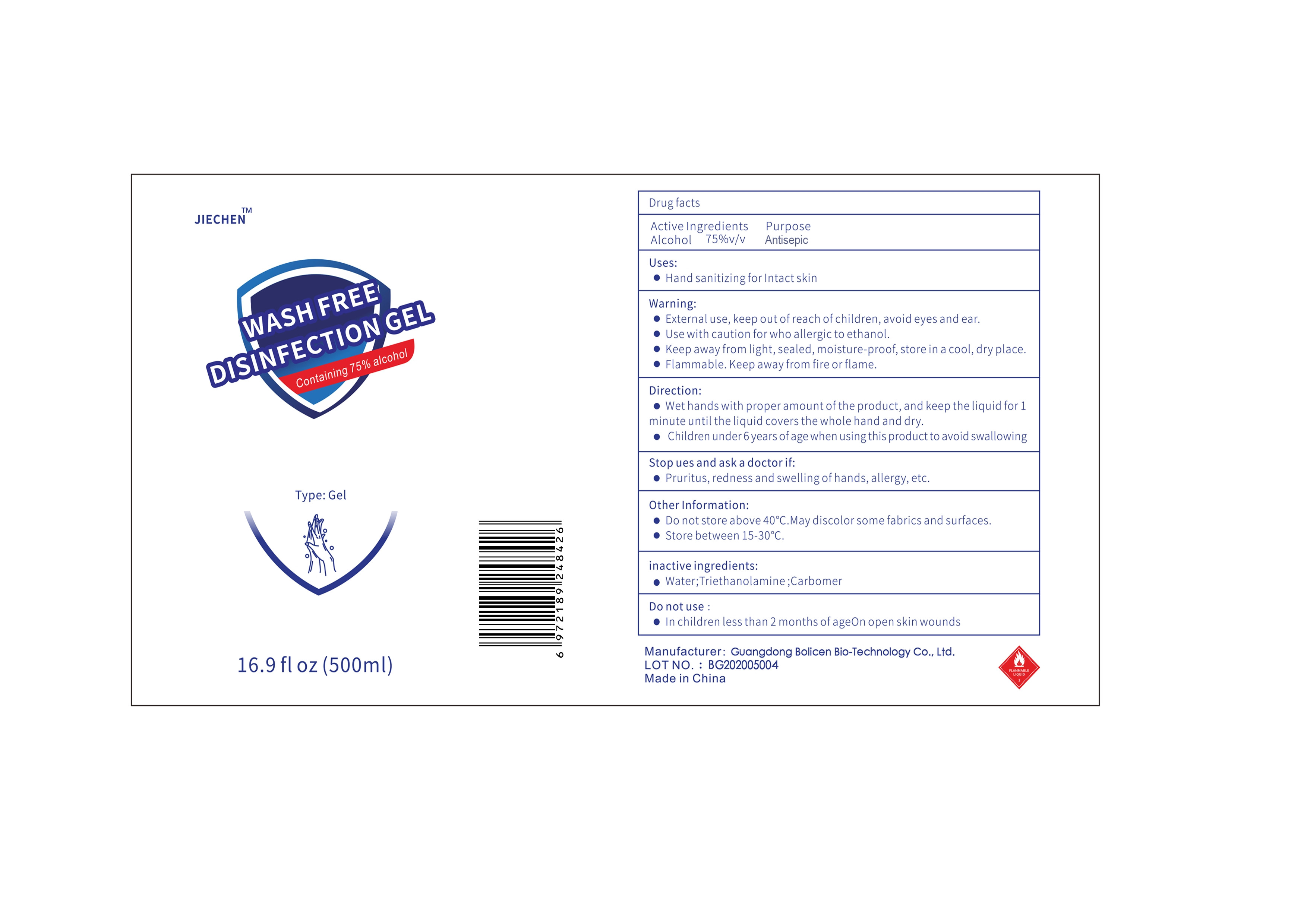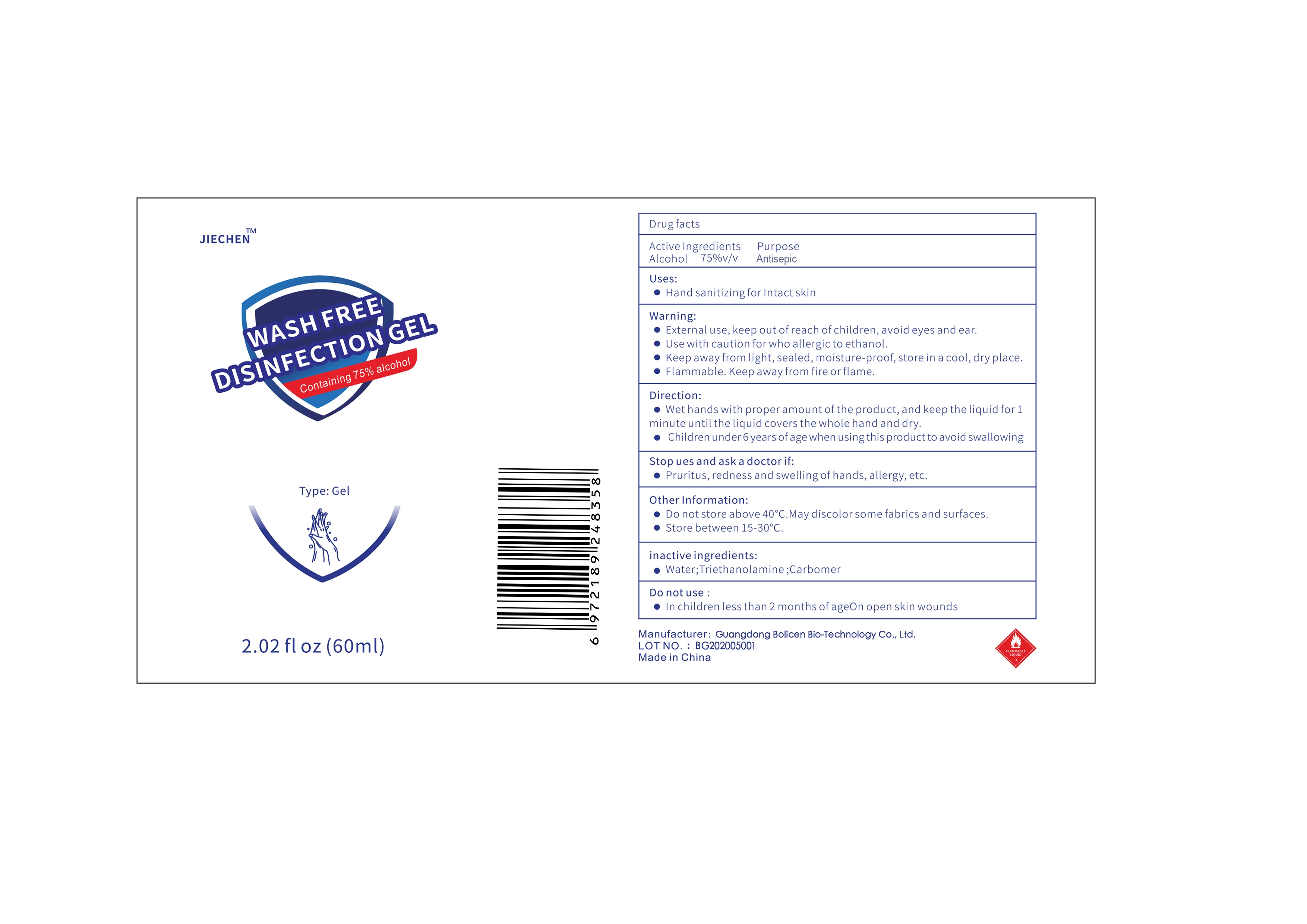 DRUG LABEL: Wash Free Disinfection
NDC: 78293-005 | Form: GEL
Manufacturer: Guangdong Bolicen Bio-Technology Co., Ltd.
Category: otc | Type: HUMAN OTC DRUG LABEL
Date: 20200710

ACTIVE INGREDIENTS: ALCOHOL 75 mL/100 mL
INACTIVE INGREDIENTS: TROLAMINE; CARBOMER HOMOPOLYMER, UNSPECIFIED TYPE; WATER

Wash Free Disinfection Gel

Active Ingredient(s)

Alcohol75%v/v

Purpose

Antiseptic

Use

Hand sanitizing for Intact skin

Warnings

External use, keep out of reach of children, avoid eyes and ear.
Use with caution for who allergic to ethanol.
Keep away from light, sealed, moisture-proof, store in a cool, dry placee.
Flammable. Keep away from fire or flame.

Do not use

In children less than 2 months of ageOn open skin wounds

WHEN USING

/

Stop ues and ask a doctor if
Pruritus, redness and swelling of hands, allergy, etc.

KEEP OUT OF REACH OF CHILDREN

Children under 6 years of age when using this product to avoid swallowing.

Directions

Wet hands with proper amount of the product, and keep the liquid for 1 minute until the liquid covers the whole hand and dry.
Children under 6 years of age when using this product to avoid swallowing.

Other information

Do not store above 40 °C. May discolor some fabrics and surfaces
Store between15-30°C

Inactive ingredients

Water, Triethanolamine, Carbomer